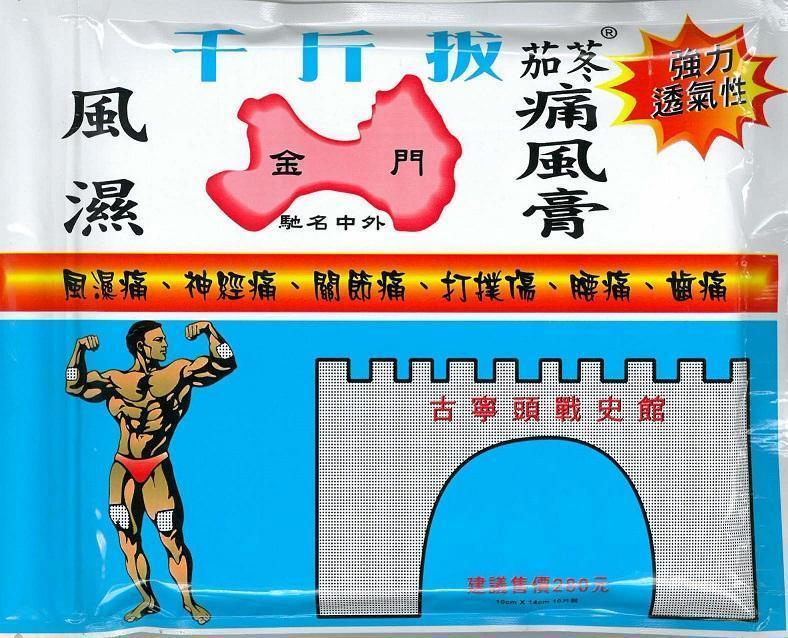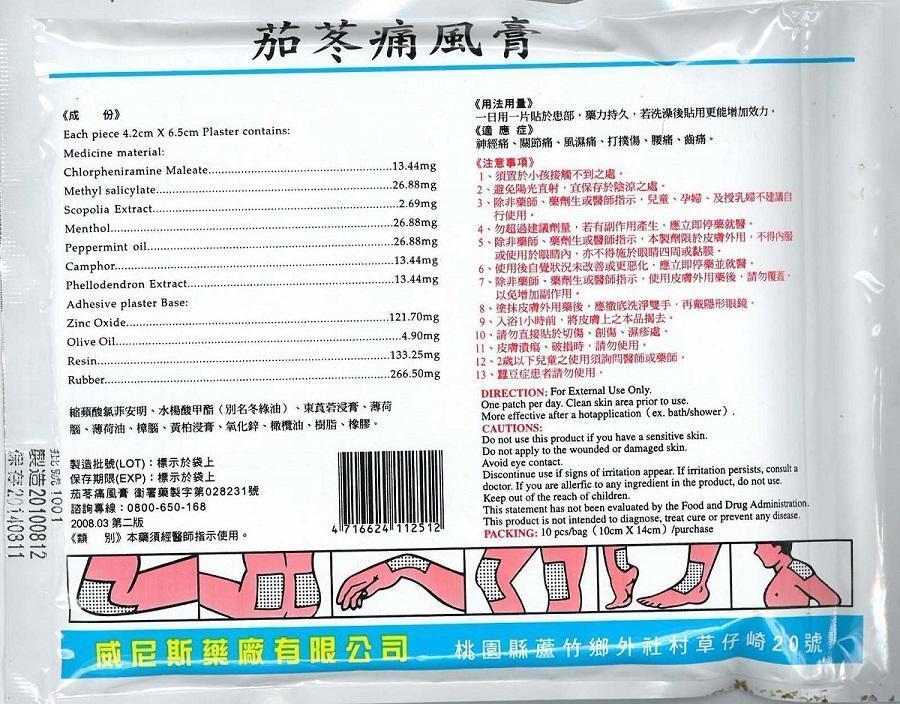 DRUG LABEL: PAIN
NDC: 69165-101 | Form: PATCH
Manufacturer: GEORGE L. RODRIGUEZ M.D., PC
Category: homeopathic | Type: HUMAN OTC DRUG LABEL
Date: 20140812

ACTIVE INGREDIENTS: CHLORPHENIRAMINE MALEATE 13.4 mg/1 1; METHYL SALICYLATE 26.9 mg/1 1; SCOPOLIA CARNIOLICA WHOLE 2.7 mg/1 1; MENTHOL 26.9 mg/1 1; PEPPERMINT OIL 26.9 mg/1 1; CAMPHOR (SYNTHETIC) 13.4 mg/1 1; PHELLODENDRON AMURENSE WHOLE 13.4 mg/1 1
INACTIVE INGREDIENTS: ZINC OXIDE; OLIVE OIL; BOSWELLIA SERRATA RESIN OIL; NATURAL LATEX RUBBER

ACTIVE INGREDIENT

EACH PIECE 4.2 CM X 6.5 CM PLASTER CONTAINS:

MEDICINAL MATERIAL:

CHLORPHENIRAMINE MALEATE.....13.44 MG

METHYL SALICYLATE.....26.88 MG

SCOPOLIA EXTRACT.....2.69 MG

MENTHOL.....26.88 MG

PEPPERMINT OIL.....26.88 MG

CAMPHOR.....13.44 MG

PHELLODENDRON EXTRACT.....13.44 MG

PURPOSE

PAIN RELIEF

WARNINGS

CAUTIONS:

DO NOT USE THIS PRODUCT IF YOU HAVE A SENSITIVE SKIN.

DO NOT APPLY TO THE WOUNDED OR DAMAGED SKIN.

AVOID EYE CONTACT.

DISCONTINUE USE IF SIGNS OF IRRITATION APPEAR. IF IRRITATION PERSISTS, CONSULT A DOCTOR. IF YOU ARE ALLERGIC TO ANY INGREDIENT IN THE PRODUCT, DO NOT USE.

INDICATIONS AND USAGE

USES: FOR THE TEMPORARY RELIEF OF MINOR ACHES AND PAINS OF MUSCLES AND JOINTS ASSOCIATED WITH ARTHRITIS, SIMPLE BACKACHE, STRAINS, SPRAINS, MUSCLE SORENESS AND STIFFNESS.

DIRECTIONS:

FOR EXTERNAL USE ONLY.

ONE PATCH PER DAY. CLEAN SKIN AREA PROR TO USE.

MORE EFFECTIVE AFTER A HOT APPLICATION (EX. BATH/SHOWER).

KEEP OUT OF REACH OF CHILDREN.

INACTIVE INGREDIENT

ADHESIVE PLASTER BASE:

ZINC OXIDE.....121.70 MG

OLIVE OIL.....4.90 MG

RESIN.....133.25 MG

RUBBER.....266.50 MG